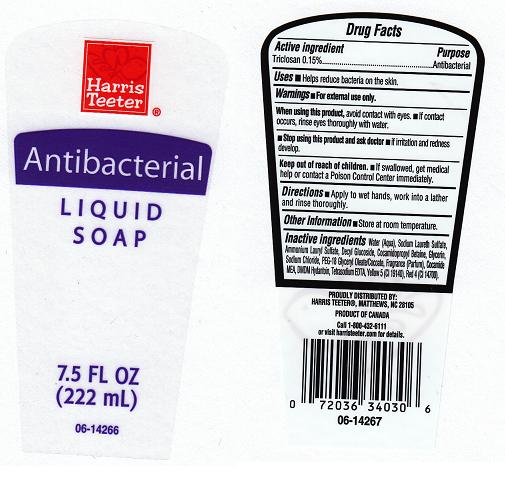 DRUG LABEL: Harris Teeter
NDC: 72036-220 | Form: SOAP
Manufacturer: HARRIS TEETER
Category: otc | Type: HUMAN OTC DRUG LABEL
Date: 20101007

ACTIVE INGREDIENTS: TRICLOSAN 0.15 mL/100 mL
INACTIVE INGREDIENTS: WATER; SODIUM LAURETH SULFATE; AMMONIUM LAURYL SULFATE; COCAMIDOPROPYL BETAINE; GLYCERIN; SODIUM CHLORIDE; COCO MONOETHANOLAMIDE; DMDM HYDANTOIN; EDETATE SODIUM; CITRIC ACID MONOHYDRATE; FD&C RED NO. 4; FD&C YELLOW NO. 5

Active Ingredient

Triclosan 0.15%

Purpose

Antibacterial

Warnings

For external use only.

When using this product

- Avoid contact with eyes. If contact occurs, rinse with water.

Stop using this product and ask doctor if

- irritation or redness develops and lasts.

Keep out of reach of children.

In case of accidental ingestion, get medical help or contact a Poison Control Center immediately.

Directions

Apply onto wet hands and work into a lather, rinse thoroughly.

Uses

To help reduce bacteria on the skin

Inactive Ingredients

Water (Aqua), Sodium Laureth Sulfate, Ammonium Lauryl Sulfate, Decyl Glucoside, Cocamidopropyl Betaine, Glycerin, Sodium Chloride, PEG-18 Glyceryl Oleate/cocoate, Fragrance (Parfum), Cocamide MEA, DMDM Hydantoin, Tetrasodium EDTA, Yellow 5 (CI 19140), Red 4 (CI 14700)

Package Front and Back Labels

ht7.5.jpg